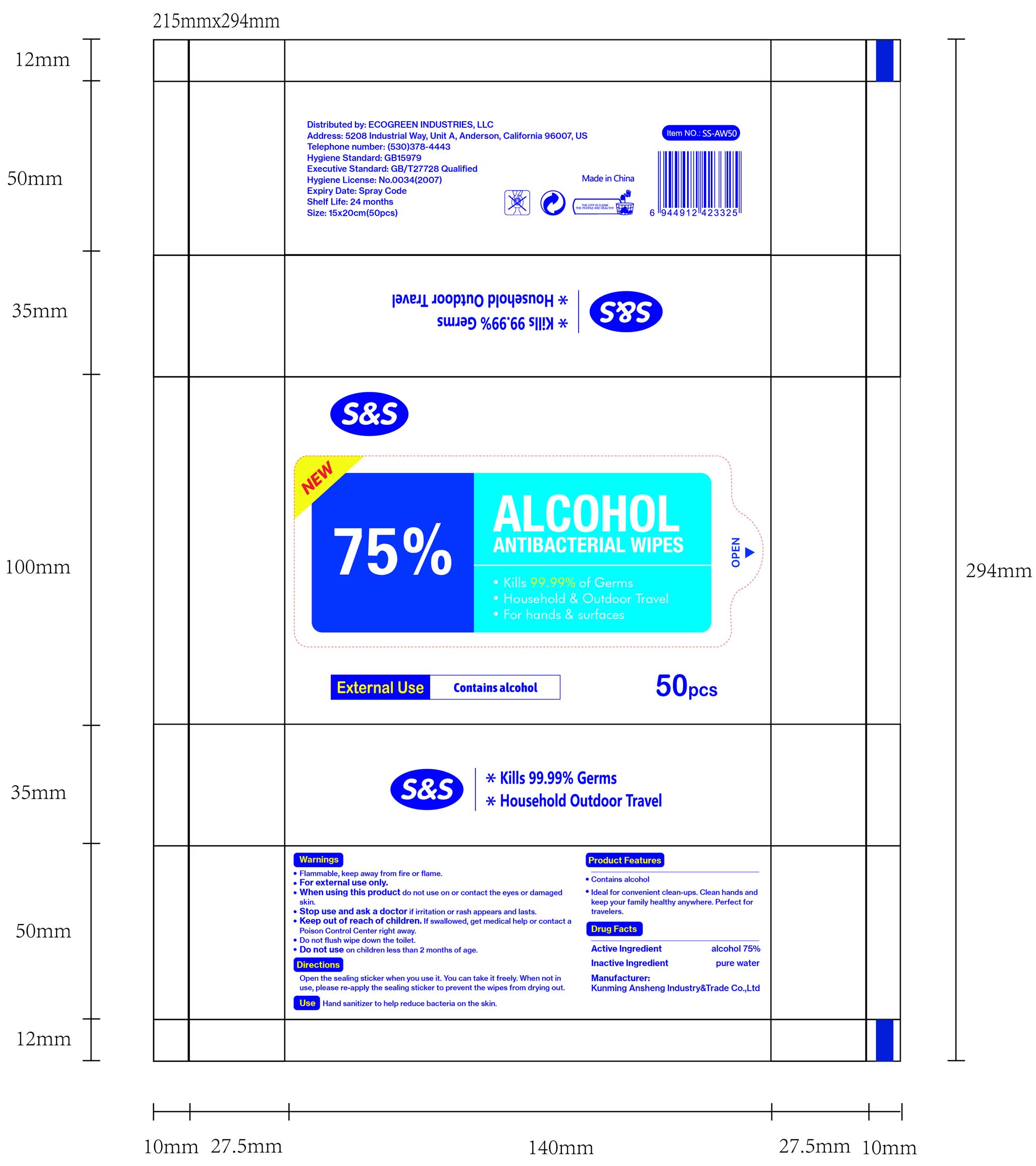 DRUG LABEL: Alcohol Antibacterial Wipes
NDC: 78183-007 | Form: CLOTH
Manufacturer: Kunming Ansheng Industry & Trade Co., Ltd.
Category: otc | Type: HUMAN OTC DRUG LABEL
Date: 20200821

ACTIVE INGREDIENTS: ALCOHOL 0.75 U/1 U
INACTIVE INGREDIENTS: WATER

75% Alcohol Wipes (S&S)

Active Ingredient(s)

Alcohol 75% v/v.

Purpose

Antibacterial; Clean hands and keep your family healthy anywhere. Perfect for travelers.

Use

Hand sanitizer to help reduce bacteria on the skin.

Warnings

For external use only. Flammable. Keep away from heat or flame

Do not use on children less than 2 months of age.

When using this product do not use in or contact the eyes or damaged skin.

Stop use and ask a doctor if irritation or rash appears and lasts.

Keep out of reach of children. If swallowed, get medical help or contact a Poison Control Center right away.

Directions

- Open the sealing sticker when you use it.
- You can take it freely.
- When not in use, please re-apply the sealing sticker to prevent the wipes from drying out.

Inactive ingredients

Pure water.

Package Label - Principal Display Panel

50 wipes in 1 Bag.

NDC: 78183-007-01;